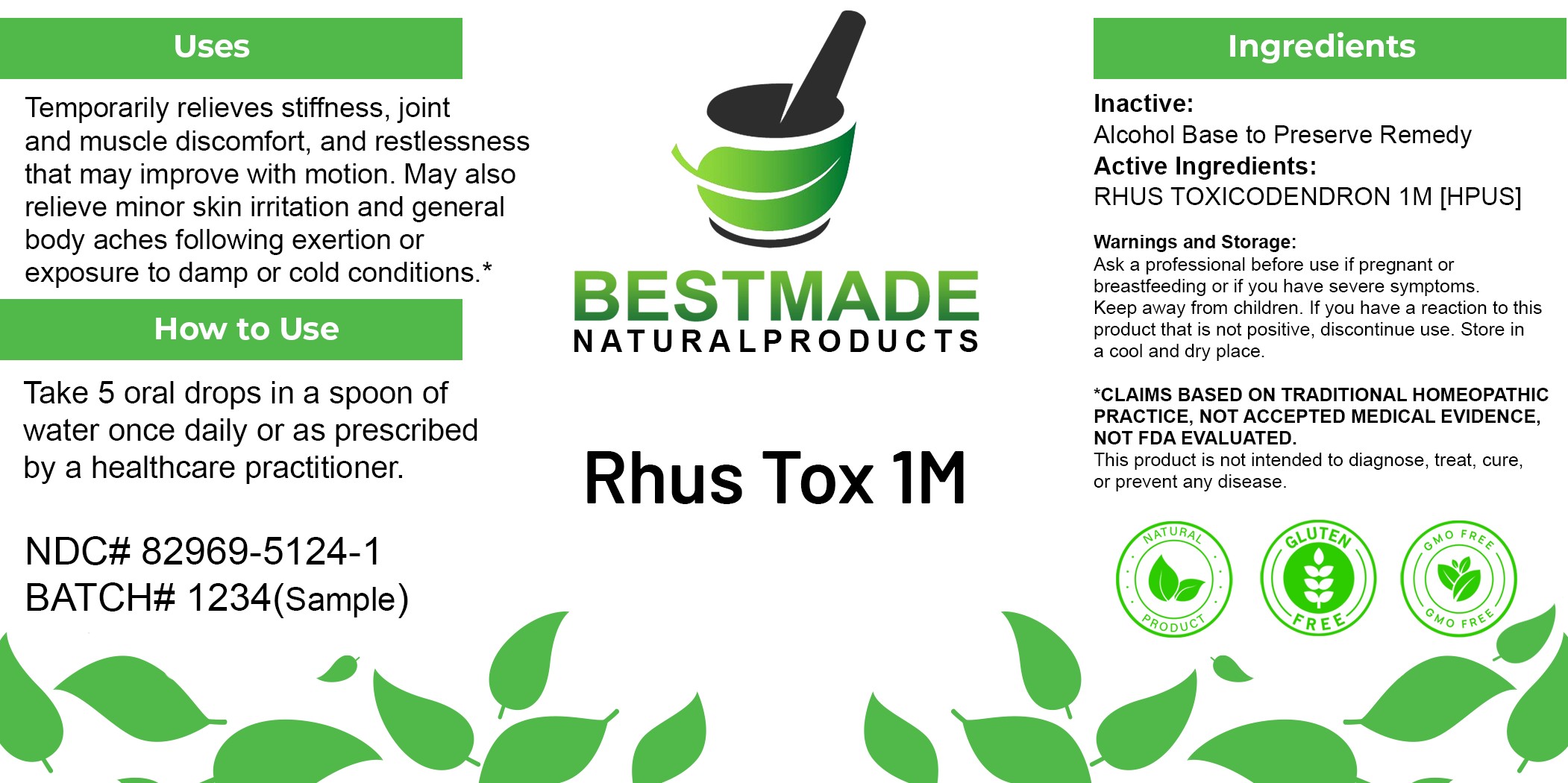 DRUG LABEL: Rhus Tox 1M
NDC: 82969-5124 | Form: LIQUID
Manufacturer: Bestmade Natural Products
Category: homeopathic | Type: HUMAN OTC DRUG LABEL
Date: 20250605

ACTIVE INGREDIENTS: TOXICODENDRON PUBESCENS LEAF 1000 [hp_C]/1 mL
INACTIVE INGREDIENTS: ALCOHOL 0.9 mL/1 mL

Rhus Tox

Inactive Ingredient: Alcohol base to preserve product.

INDICATIONS AND USAGE

Use: Temporarily relieves stiffness, joint and muscle discomfort, and restlessness that may improve with motion. May also relieve minor skin irritation and general body aches following exertion or exposure to damp or cold conditions.*

PURPOSE

Use: Temporarily relieves stiffness, joint and muscle discomfort, and restlessness that may improve with motion. May also relieve minor skin irritation and general body aches following exertion or exposure to damp or cold conditions.*

DOSAGE AND ADMINISTRATION

Dosage Instructions: Take 5 oral drops in a spoon of water once daily or as prescribed by a healthcare practitioner.

Active Ingredient: RHUS TOXICODENDRON 1M [HPUS]

KEEP OUT OF REACH OF CHILDREN

Warnings and Storage:

This product is classified as a high-potency homeopathic remedy and is to be used as advised by health care professional. Ask a professional before use if pregnant or breastfeeding or if you have severe symptoms. Keep away from children. If you have a reaction to this product that is not positive, discontinue use. Store in a cool and dry place.

*CLAIMS BASED ON TRADITIONAL HOMEOPATHIC PRACTICE, NOT ACCEPTED MEDICAL EVIDENCE, NOT FDA EVALUATED. This product is not intended to diagnose, treat, cure, or prevent any disease.

Warnings and Storage:

This product is classified as a high-potency homeopathic remedy and is to be used as advised by health care professional. Ask a professional before use if pregnant or breastfeeding or if you have severe symptoms. Keep away from children. If you have a reaction to this product that is not positive, discontinue use. Store in a cool and dry place.

*CLAIMS BASED ON TRADITIONAL HOMEOPATHIC PRACTICE, NOT ACCEPTED MEDICAL EVIDENCE, NOT FDA EVALUATED. This product is not intended to diagnose, treat, cure, or prevent any disease.

Entire product label